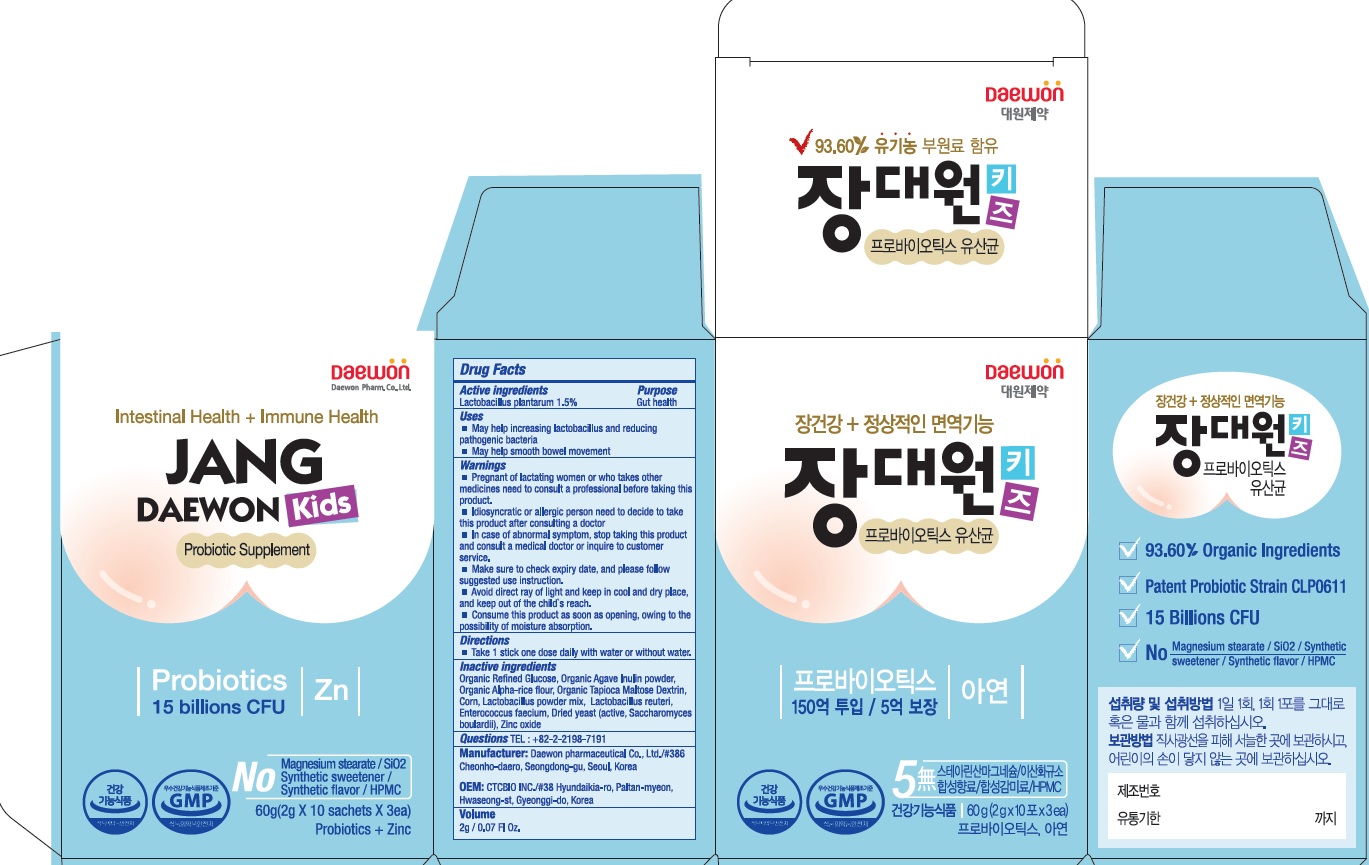 DRUG LABEL: Jangdaewon Probiotics Kids
NDC: 72460-700 | Form: POWDER
Manufacturer: Daewon Pharmaceutical Co., Ltd.
Category: otc | Type: HUMAN OTC DRUG LABEL
Date: 20190313

ACTIVE INGREDIENTS: Lactobacillus plantarum 30 mg/2 g
INACTIVE INGREDIENTS: Lactobacillus reuteri

ACTIVE INGREDIENT

Active ingredients: Lactobacillus plantarum 1.5%

INACTIVE INGREDIENT

Inactive ingredients:

Organic Refined Glucose, Organic Agave Inulin powder, Organic Alpha-rice flour, Organic Tapioca Maltose Dextrin, Corn, Lactobacillus powder mix, Lactobacillus reuteri, Enterococcus faecium, Dried yeast (active, Saccharomyces boulardii), Zinc oxide

PURPOSE

Purpose: Gut health

WARNINGS

■ Pregnant of lactating women or who takes other medicines need to consult a professional before taking this product.
■ Idiosyncratic or allergic person need to decide to take this product after consulting a doctor
■ In case of abnormal symptom, stop taking this product and consult a medical doctor or inquire to customer service.
■ Make sure to check expiry date, and please follow suggested use instruction.
■ Avoid direct ray of light and keep in cool and dry place, and keep out of the child's reach.
■ Consume this product as soon as opening, owing to the possibility of moisture absorption.

KEEP OUT OF REACH OF CHILDREN

Keep out of the child's reach.

Uses

■ May help increasing lactobacillus and reducing pathogenic bacteria
■ May help smooth bowel movement

Directions

■ Take 1 stick one dose daily with water or without water.